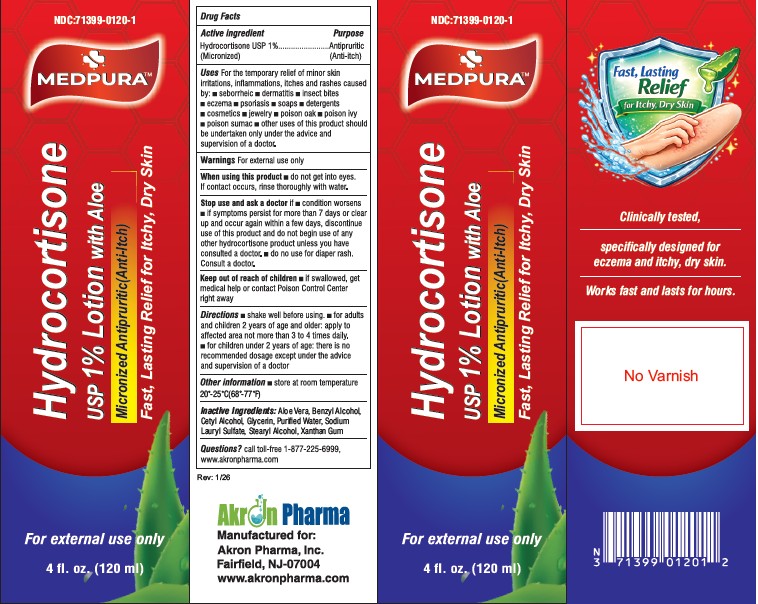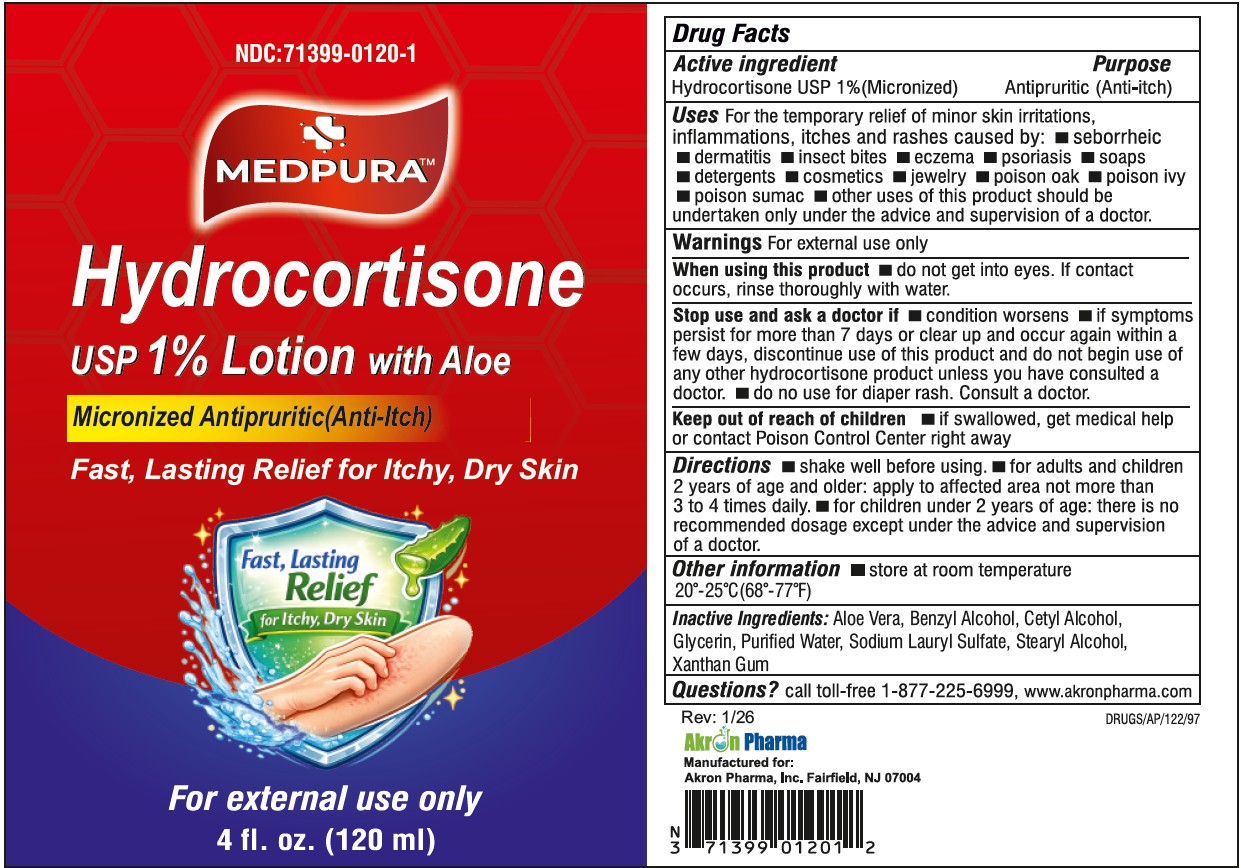 DRUG LABEL: Hydrocortisone
NDC: 71399-0120 | Form: LOTION
Manufacturer: AKRON PHARMA INC
Category: otc | Type: HUMAN OTC DRUG LABEL
Date: 20260112

ACTIVE INGREDIENTS: HYDROCORTISONE 10 mg/1 mL
INACTIVE INGREDIENTS: WATER; GLYCERIN; CETYL ALCOHOL; BENZYL ALCOHOL; SODIUM LAURYL SULFATE; STEARYL ALCOHOL; ALOE VERA LEAF; XANTHAN GUM

Hydrocortisone USP 1% Lotion
Drug Facts

Active Ingredient

Hydrocortisone 1% (Micronized)

Purpose

Antipruritic (Anti-itch)

Use

For the temporary relief of minor skin irritations, inflammations, itching and rashes caused by:

- insect bites
- eczema
- psoriasis
- soaps
- detergents
- cosmetics,
- jewelry,
- poison oak,
- poison sumac
- Other uses of this product should be undertaken only under the advice and supervision of a doctor.

Warnings

For external use only.

When using this product

Do not get into eyes. If contact occurs, rinse thoroughly with water.

Stop use and ask a doctor if

- Condition worsens
- If symptoms persist for more than 7 days or clear up and occur again within a few days. Discontinue use of this product and do not begin use of any other hydrocortisone product unless you have consulted a doctor.
- Do no use for diaper rash. Consult a doctor.

Keep out of Reach of Children

Keep out of the reach of children. If swallowed, get medical help or contact Poison Control Center right away.

Directions

- Shake will before using.
- For adults and children 2 years of age and older: Apply to affected area not more than 2 to 4 times daily.
- For children under 2 years of age: there is no recommended dosage except under the advice and supervision of a doctor.

Other Information

• Store away from excessive heat or cold. Shake well before using.

Inactive Ingredients

Purified Water, Glycerin, Cetyl Alcohol, Benzyl Alcohol, Sodium Lauryl Sulfate, Stearyl Alcohol, Aloevera, Xanthan Gum

Questions?

Please Call 1(877) 225-6999

Manufactured for:

Akron Pharma, Inc.
Fairfield, NJ 07004

Rev. 03/19

Manufactured in U.S.A